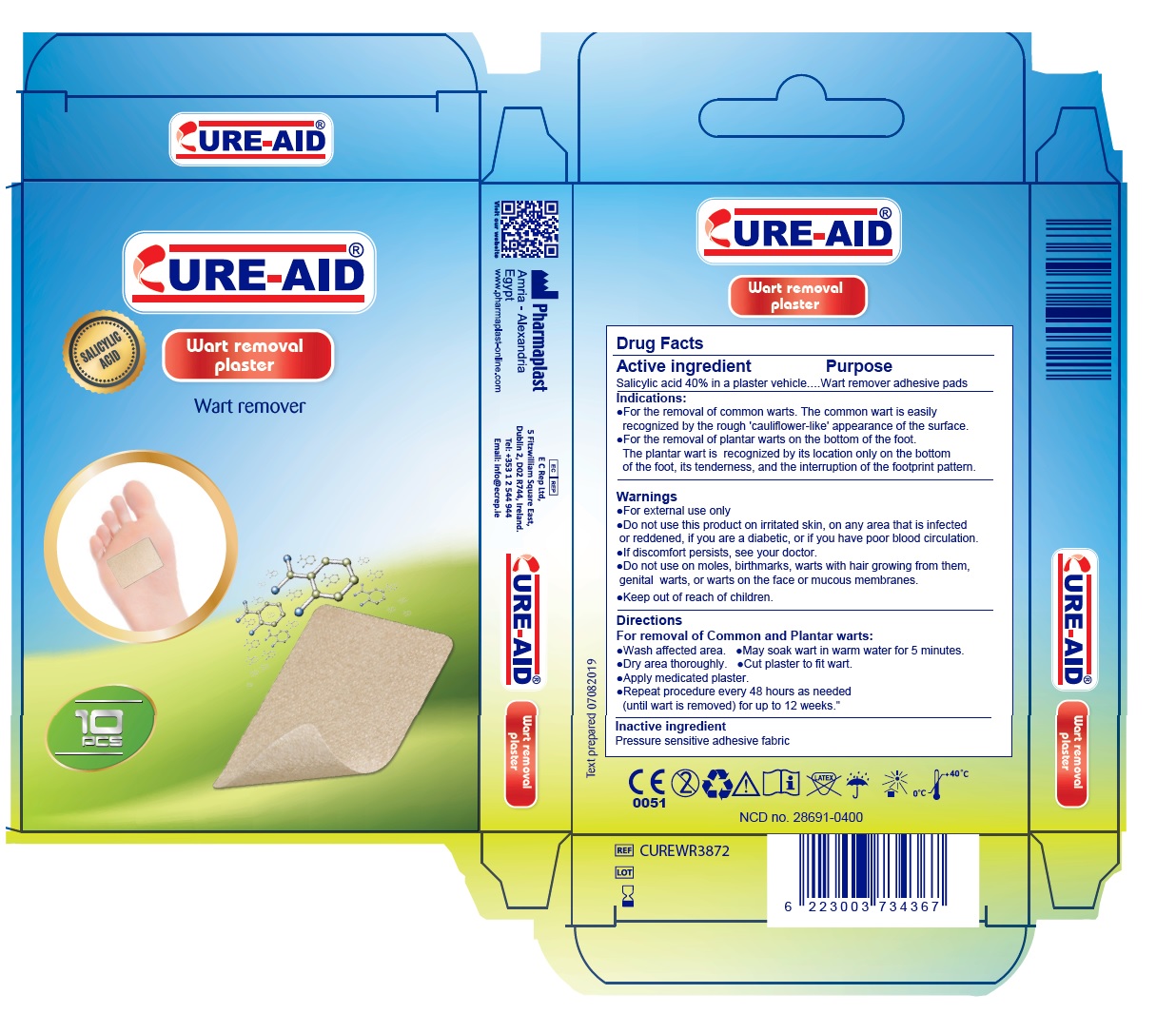 DRUG LABEL: Wart Remover
NDC: 28691-0400 | Form: PLASTER
Manufacturer: Pharmaplast SAE
Category: otc | Type: HUMAN OTC DRUG LABEL
Date: 20250107

ACTIVE INGREDIENTS: SALICYLIC ACID 0.4 g/1 1
INACTIVE INGREDIENTS: NATURAL LATEX RUBBER; SILICON DIOXIDE; POLYISOBUTYLENE (75000 MW); PENTAERYTHRITOL TETRAKIS(3-(3,5-DI-TERT-BUTYL-4-HYDROXYPHENYL)PROPIONATE)

Wart remover plaster

Active ingredient

Salicylic acid 40% in a plaster vehicle

Purpose

Wart remover adhesive pads

Indications:

- For the removal of common warts. The common wart is easily recognized by the rough 'cauliflower-like' appearance of the surface.
- For the removal of plantar warts on the bottom of the foot.
  The plantar wart is recognized by its location only on the bottom of the foot, its tenderness, and the interruption of the footprint pattern.

Warnings

- For external use only
- Do not use this product on irritated skin, on any area that is infected or reddened, if you are a diabetic, or if you have poor blood circulation.
- If discomfort persists, see your doctor.
- Do not use on moles, birthmarks, warts with hair growing from them, genital warts, or warts on the face or mucous membranes.

- Keep out of reach of children.

Directions

For removal of Common and Plantar warts:

- Wash affected area.
- May soak wart in warm water for 5 minutes.
- Dry area thoroughly.
- Cut plaster to fit wart.
- Apply medicated plaster.
- Repeat procedure every 48 hours as needed (until wart is removed) for up to 12 weeks.

Inactive ingredient

Pressure sensitive adhesive fabric

CURE-AID®

Pharmaplast

Amria – Alexandria
Egypt
www.Pharmaplast-online.com